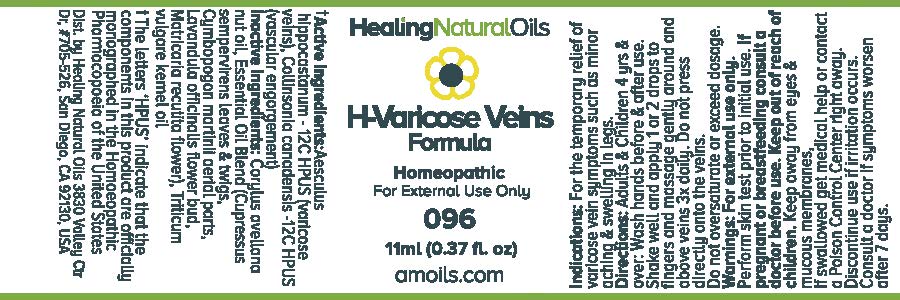 DRUG LABEL: H-Varicose Veins Formula
                
NDC: 61077-096 | Form: OIL
Manufacturer: Healing Natural Oils LLC
Category: homeopathic | Type: HUMAN OTC DRUG LABEL
Date: 20171227

ACTIVE INGREDIENTS: HORSE CHESTNUT 12 [hp_C]/11 mL; COLLINSONIA CANADENSIS ROOT 12 [hp_C]/11 mL
INACTIVE INGREDIENTS: EUROPEAN HAZELNUT OIL; CUPRESSUS SEMPERVIRENS LEAFY TWIG; CYMBOPOGON FLEXUOSUS WHOLE; LAVANDULA ANGUSTIFOLIA FLOWER; CHAMOMILE; WHEAT GERM OIL

Active Ingredients:

Aesculus hippocastanum-12C HPUS,
Collinsonia canadensis -12C HPUS,

Purpose

Aesculus hippocastanum-12C HPUS (varicose veins),
Collinsonia canadensis -12C HPUS (vascular engorgement)
The letters ‘HPUS’ indicate that the components in this product are officially
monographed in the Homoeopathic Pharmacopoeia of the United States

Inactive Ingredients:

Corylus  avellana nut oil,  Essential  Oil  Blend (Cupressus
sempervirens leaves and twigs, Cymbopogon  martinii  aerial parts, Lavandula officinalis
flower bud, Matricaria recutita flower), Triticum vulgare kernel oil

Indications:

For the temporary relief of varicose vein symptoms such as minor aching and swelling in legs.

Directions:

Adults and Children 4 yrs and over: Wash hands before and after use.
Shake well and apply 1 or 2 drops to fingers and massage gently around and above veins 3x daily. Do not press directly onto the veins.
Do not oversaturate or exceed dosage.

Warnings:

For external use only.

Perform skin test prior to initial use.

PREGNANCY OR BREAST FEEDING

If pregnant or breastfeeding consult a doctor before use.

Keep out of reach of children.

OTHER SAFETY INFORMATION

Keep away from eyes and mucous membranes. If swallowed get medical help
or contact a Poison Control Center right away.

Discontinue use if irritation occurs.

ASK DOCTOR

Consult a doctor if symptoms worsen after 7 days.

DESCRIPTION

Dist. by Healing Natural Oils 3830 Valley Ctr Dr, #705-526, San Diego, CA 92130, USA

PACKAGE LABEL

Healing Natural Oils

H-Varicose Veins
Formula

Homeopathic

For External Use Only

096

11ml (0.37 fl. oz)
amoils.com